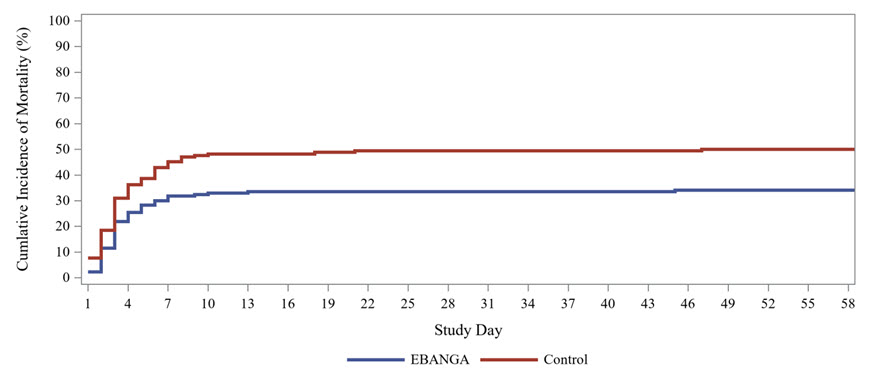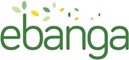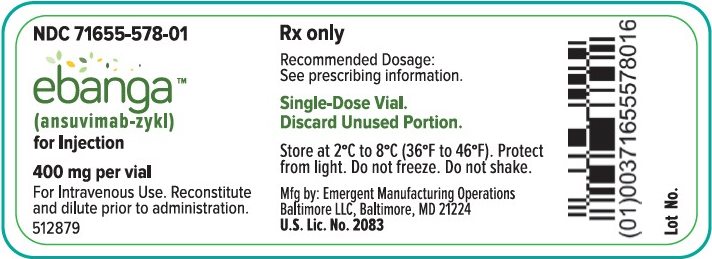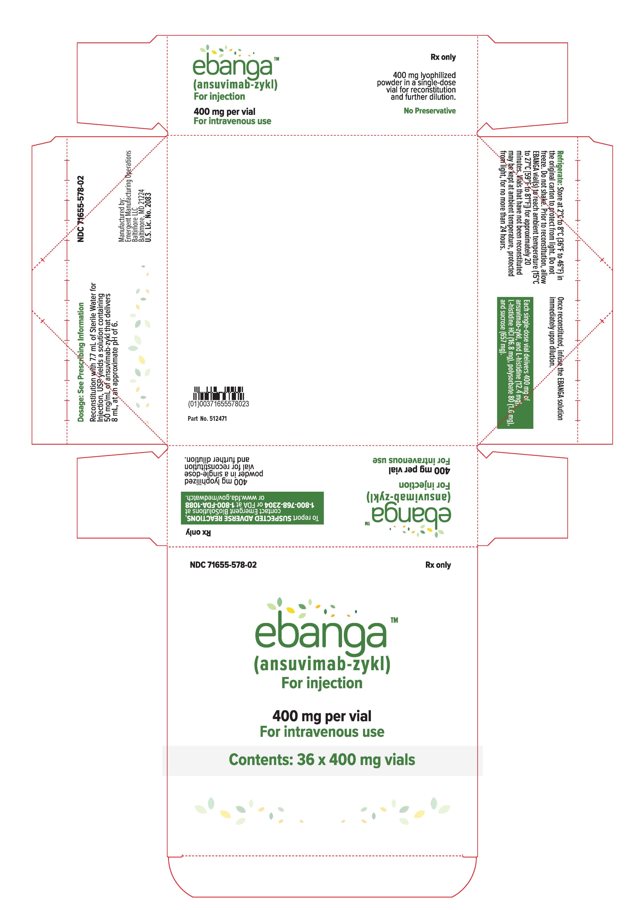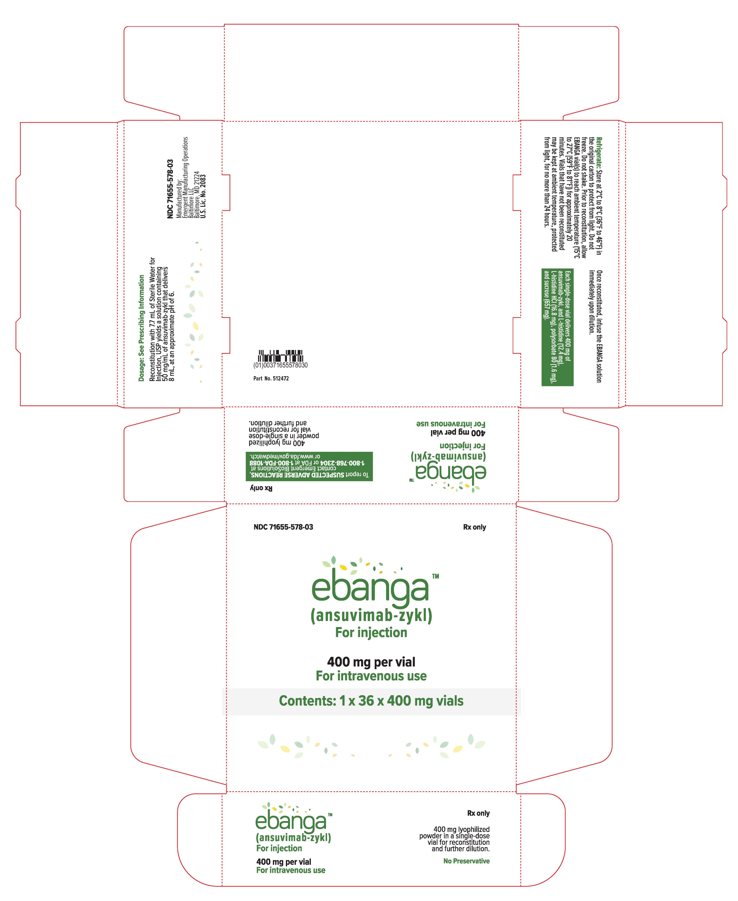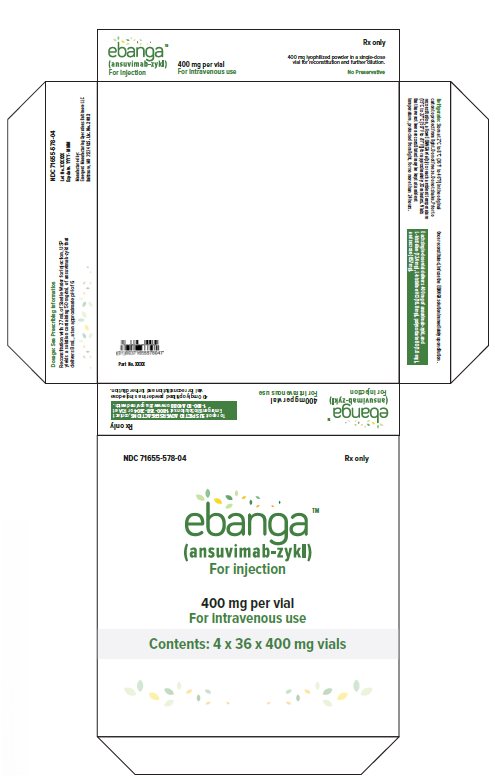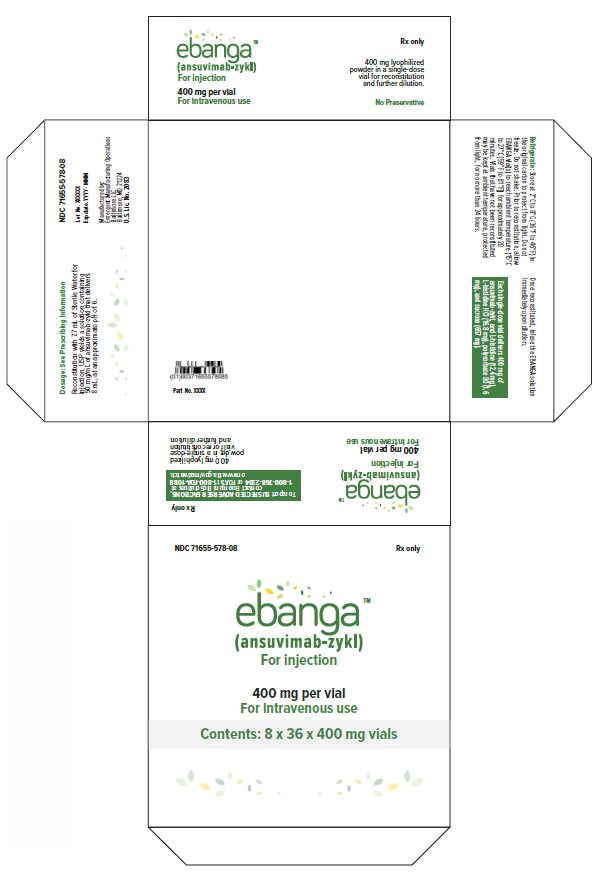 DRUG LABEL: Ebanga
NDC: 71655-578 | Form: INJECTION, POWDER, LYOPHILIZED, FOR SOLUTION
Manufacturer: Emergent Manufacturing Operations Baltimore, LLC
Category: prescription | Type: HUMAN PRESCRIPTION DRUG LABEL
Date: 20260220

ACTIVE INGREDIENTS: ANSUVIMAB 400 mg/8 mL

HIGHLIGHTS OF PRESCRIBING INFORMATION

These highlights do not include all the information needed to use EBANGA™ safely and effectively. See full prescribing information for EBANGA.
EBANGATM (ansuvimab-zykl) for injection, for intravenous use
Initial U.S. Approval: 2020

1 INDICATIONS AND USAGE

EBANGA (ansuvimab-zykl) is an Orthoebolavirus zairense glycoprotein (EBOV GP)-directed human monoclonal antibody indicated for the treatment of infection caused by Orthoebolavirus zairense in adult and pediatric patients, including neonates born to a mother who is RT-PCR positive for Orthoebolavirus zairense infection. (1)

Limitation of Use

- The efficacy of EBANGA has not been established for other species of the Orthoebolavirus and Orthomarburgvirus genera.
- Orthoebolavirus zairense can change over time, and factors such as emergence of resistance or changes in viral virulence could diminish the clinical benefit of antiviral drugs. Consider available information on drug susceptibility patterns for circulating Orthoebolavirus zairense strains when deciding whether to use EBANGA.

2 DOSAGE AND ADMINISTRATION

The recommended dose of EBANGA for adult and pediatric patients is 50 mg/kg reconstituted, further diluted, and administered as a single intravenous infusion over 60 minutes. (2.1, 2.2)

See Full Prescribing Information for instructions on preparation, dilution and administration of EBANGA injection. (2.2)

3 DOSAGE FORMS AND STRENGTHS

For injection: 400 mg lyophilized powder in a single-dose vial for reconstitution and further dilution. (3)

4 CONTRAINDICATIONS

None.

5 WARNINGS AND PRECAUTIONS

Hypersensitivity Reactions Including Infusion-Associated Events: Hypersensitivity reactions including infusion-associated events have been reported with EBANGA. These may include acute, life- threatening reactions during and after the infusion. Monitor patients and in the case of severe or life-threatening hypersensitivity reactions, discontinue the administration of EBANGA immediately and administer appropriate emergency care. (5.1)

6 ADVERSE REACTIONS

The most frequently reported adverse events (≥ 5%) after administration of EBANGA were pyrexia, tachycardia, diarrhea, vomiting, hypotension, tachypnea, and chills. (6.1)

To report SUSPECTED ADVERSE REACTIONS, contact Emergent BioSolutions at 1-800-768-2304 or FDA at 1-800-FDA-1088 or www.fda.gov/medwatch.

7 DRUG INTERACTIONS

Interaction with live vaccine indicated for prevention of Orthoebolavirus zairense infection: No vaccine interaction studies have been performed.

EBANGA may reduce the efficacy of the live vaccine. The interval between administration of EBANGA therapy and live vaccination should be in accordance with current vaccination guidelines. (7.1)

8 USE IN SPECIFIC POPULATIONS

Lactation: Patients infected with Orthoebolavirus zairense should be instructed not to breastfeed due to the potential for Orthoebolavirus zairense transmission. (8.2)

FULL PRESCRIBING INFORMATION

1 INDICATIONS AND USAGE

EBANGA is indicated for the treatment of infection caused by Orthoebolavirus zairense (formerly Zaire ebolavirus) in adult and pediatric patients, including neonates born to a mother who is RT-PCR positive for Orthoebolavirus zairense infection [see Dosage and Administration (2.2) and Clinical Studies (14)].

Limitations of Use:

The efficacy of EBANGA has not been established for other species of the Orthoebolavirus and Orthomarburgvirus genera.

Orthoebolavirus zairense can change over time, and factors such as emergence of resistance, or changes in viral virulence could diminish the clinical benefit of antiviral drugs. Consider available information on drug susceptibility patterns for circulating Orthoebolavirus zairense strains when deciding whether to use EBANGA.

2 DOSAGE AND ADMINISTRATION

2.1 Recommended Dosage for Adult and Pediatric Patients

The recommended dosage of EBANGA is 50 mg/kg administered as a single intravenous (IV) infusion over 60 minutes. EBANGA must be reconstituted with Sterile Water for Injection, USP then further diluted in 0.9% Sodium Chloride Injection, USP or 5% Dextrose Injection, USP prior to IV infusion [see Dosage and Administration (2.2)].

2.2. Preparation, Administration, and Storage Instructions

EBANGA must be prepared and administered under the supervision of a health care professional.

Reconstitution Instructions

- Aseptically reconstitute and further dilute EBANGA prior to IV infusion. Do not administer as an IV push or bolus.
- More than one vial may be needed for a full dose. Calculate the dose (mg) based on the patient’s actual weight in kg and the number of EBANGA vials required [see Dosage and Administration (2.1)].
- Prior to reconstitution, allow EBANGA vial(s) to reach ambient temperature (15°C to 27°C [59°F to 81°F]) for approximately 20 minutes. If for any reason reconstitution cannot proceed immediately upon reaching ambient temperature, vials that have NOT been reconstituted may be kept at ambient temperature, protected from light, for no more than 24 hours.
- Immediately upon reaching ambient temperature, use a sterile 10 mL syringe and an 18-gauge needle to withdraw 7.7 mL of Sterile Water for Injection, USP. Insert the needle tip into the EBANGA vial. Holding horizontally, angle the needle down at an approximate 45° angle, above the lyophilized powder, which has a cake-like appearance. Slowly inject the diluent along the wall of the vial and without any air to avoid foaming and bubbles.
- Gently swirl (do NOT shake) for approximately 10 seconds; then set the vial down to rest for at least 10 seconds. Repeat until the cake is dissolved. This may take up to 20 minutes.
- Upon reconstitution, one vial delivers 8 mL of solution that is clear to slightly opalescent and colorless to slightly yellow containing 50 mg/mL of ansuvimab-zykl. Do NOT administer and discard the vial if the reconstituted solution is discolored or contains visible particles.
- Dilute the EBANGA solution immediately upon reconstitution. If needed, the reconstituted solution may be stored refrigerated at 2°C to 8°C (36°F to 46°F), protected from light, for up to 4 hours. This 4-hour window includes time required for further dilution and EBANGA solution should be infused immediately upon further dilution.

Dilution Instructions

- Following reconstitution, EBANGA must be further diluted prior to IV infusion.
  - Use an 18-20 gauge, 1-1.5” needle with an appropriately sized syringe up to 60 mL to perform the dilution steps.
  - Prepare the EBANGA IV dosing solution using an appropriately sized syringe up to 60 mL.
- For patients weighing ≥ 2 kg, prepare the diluent using either a latex-free, di-ethylhexylphthalate (DEHP)-free 0.9% Sodium Chloride Injection USP infusion bag, or latex-free, DEHP-free 5% Dextrose Injection USP infusion bag. For patients weighing 0.5 to < 2 kg use a pump-compatible syringe (Table 1).
  - For adult and pediatric patients, either 0.9% Sodium Chloride Injection, USP or 5% Dextrose Injection, USP can be used as the diluent.
  - The total volume of the infusion solution to be administered is based on the patient’s body weight and is specified in Table 1.

For patients weighing 0.5 to < 2 kg:

  - Use a 10 mL syringe compatible with the IV infusion pump.
  - Fill the 10 mL syringe with the appropriate amount of diluent (Table 1).
  - Add the calculated volume of EBANGA to the 10 mL syringe (Table 1).
  - Mix the diluted solution by gentle inversion (3 to 5 times) until admixed. Do not shake.

For patients weighing ≥ 2 kg:

  - Select a diluent solution infusion bag size of appropriate fill volume based on the patient’s body weight (see Table 1).
  - Withdraw and discard from the bag a volume of diluent solution that will leave remaining in the bag the appropriate volume based on the patient’s weight (see Table 1). Then add the calculated volume of EBANGA to the bag based on the patient's weight (see Table 1).
    For example, for a 55 kg patient, withdraw and discard 150 mL of diluent from a 250 mL infusion bag. Then add 55 mL of EBANGA to obtain a total infusion volume of 155 mL.
  - Gently invert the IV bag 5 to 10 times until the diluted solution is admixed. Do NOT shake.
- Infuse the EBANGA solution immediately upon dilution. If needed, the diluted infusion solution may be stored refrigerated at 2°C to 8°C (36°F to 46°F), for up to 4 hours. Do not freeze the diluted solution. If refrigerated, allow approximately 20 minutes for the diluted solution to come to ambient temperature prior to use. These time limits include reconstitution time.
  Prepare a medical label including patient weight in kg, date, and time of reconstitution.
- Discard vial(s) and all unused contents.

Table 1 EBANGA Volume, Diluent Volume and Total Infusion Volume by Body Weight
Weight in kg | Volume of EBANGA | Diluent Volume (mL)a,b | Final Infusion Volume (mL) | Syringe or Infusion Bag Volume for IV Administration
0.5 kg | 1 mL/kg | 2.5 mL | 3 mL | 10 mL syringe compatible with IV infusion pump
1 kg | 1 mL/kg | 5 mL | 6 mL | 10 mL syringe compatible with IV infusion pump
2 to 10 kg | 1 mL/kg | 10 mL | 12 to 20 mL | 25 mL IV bag
11 to 25 kg | 1 mL/kg | 25 mL | 36 to 50 mL | 50 mL IV bag
26 to 50 kg | 1 mL/kg | 50 mL | 76 to 100 mL | 100 mL IV bag
51 to 100 kg | 1 mL/kg | 100 mL | 151 to 200 mL | 250 mL IV bag
101 kg and above | 1 mL/kg | 150 mL | 251 mL and above | 500 mL IV bag
a The recommended diluent volume ensures the final concentration of the diluted solution is approximately 8-30 mg/mL.
b For IV bag administration, the diluent volume column includes the volume of diluent needed to remain in the infusion bag.

Administration

- Parenteral drug products should be inspected visually for particulate matter and discoloration prior to administration. Do not administer if discolored or if the vial contains visible particles.
- Do not mix with or administer as an infusion with other medicinal products.
- Prepare the IV infusion line with 1.2 micron in-line filter extension set.
- Administer the IV infusion solution over 60 minutes.
  - The diluted EBANGA IV solution can be infused via a central line or peripheral catheter. Do not administer EBANGA as an IV push or bolus.
  - Do not co-administer other drugs simultaneously through the same infusion line.
  - Infusions may be slowed or stopped if necessary, to alleviate any side effects.
- At the end of the infusion, if a syringe pump was used, then remove the syringe and flush the line with 2 to 5 mL of diluent, but not to exceed the total infusion volume. If an infusion bag was used, replace the empty bag and flush the line by infusing at least 25 mL of the diluent, to ensure complete product administration.

3 DOSAGE FORMS AND STRENGTHS

For injection: 400 mg of ansuvimab-zykl, available as an off-white to white lyophilized powder in single-dose vial for reconstitution and further dilution.

4 CONTRAINDICATIONS

None.

5 WARNINGS AND PRECAUTIONS

5.1 Hypersensitivity Reactions Including Infusion-Associated Events

Hypersensitivity reactions including infusion-associated events have been reported with EBANGA. These may include acute, life-threatening reactions during and after the infusion. Monitor all patients for signs and symptoms including, but not limited to, hypotension, chills and elevation of fever, during and following EBANGA infusion. In the case of severe or life-threatening hypersensitivity reactions, discontinue the administration of EBANGA immediately and administer appropriate emergency care [see Adverse Reactions (6.1)].

Infusion could not be completed in 1% of participants who received EBANGA due to infusion-associated adverse events. The rate of infusion of EBANGA may be slowed or interrupted if the patient develops any signs of infusion-associated events or other adverse events [see Adverse Reactions (6.1)].

6 ADVERSE REACTIONS

The following clinically significant adverse reactions are described elsewhere in the labeling:

- Hypersensitivity Reactions Including Infusion-Associated Events [see Warnings and Precautions (5.1)]

6.1 Clinical Trials Experience

Because clinical trials are conducted under widely varying conditions, adverse reaction rates observed in the clinical trials may not reflect the rates observed in practice.

Overall, 424 adult and pediatric participants with Orthoebolavirus zairense infection received EBANGA in one clinical trial and as part of an expanded access program during the 2018 Orthoebolavirus zairense outbreak in the Democratic Republic of Congo (DRC).

In the PALM trial, the safety of EBANGA was evaluated in a multi-center, open-label, randomized controlled trial, in which 173 participants (119 adults and 54 pediatric participants) with confirmed Orthoebolavirus zairense infection received EBANGA as a single 50 mg/kg IV infusion and 168 participants received an investigational control [see Clinical Studies (14)]. All participants received optimized standard of care treatment (oSOC). The median age of the study population that received EBANGA was 26 years (range: 1 day to 85 years) and 55% were female.

During the same outbreak, 251 participants (173 adults and 78 pediatric participants) with laboratory-confirmed Orthoebolavirus zairense infection received EBANGA under an expanded access program, 57% of whom were female. Ages ranged from 6 days to 80 years, with a median age of 25 years.

Common Adverse Events

Table 2 summarizes the adverse events that were reported in the PALM trial from a pre-defined list of signs and symptoms that occurred during EBANGA infusion. The evaluation of adverse events in participants who received EBANGA may have been confounded by the signs and symptoms of the underlying Orthoebolavirus zairense infection. Twenty nine percent (n=51) of participants who received EBANGA in the PALM Trial experienced a pre-specified infusion-related adverse event. The most common pre-specified infusion-related adverse event reported in at least 10% of participants who received EBANGA was fever (Table 2). The adverse event profile in adult and pediatric participants treated with EBANGA was similar.

Table 2 Adverse Events That Occurred During Infusion in >10% of Adult and Pediatric Participants in the PALM Trial
Adverse Eventa | EBANGA (N=173) % | Controlb (N=168) %
Pyrexia | 17 | 58
Tachycardia | 9 | 32
Diarrheac | 9 | 18
Vomitingc | 8 | 23
Hypotension | 8 | 31
Tachypnea | 6 | 28
Chillsd | 5 | 33
Hypoxiac | 3 | 11
a Adverse events in this table were reported on the day of infusion, and included signs and symptoms that occurred during or immediately after infusion
b Investigational therapy administered as three separate infusions
c Adverse events that occurred during infusion but were not pre-specified.
d The term chills includes other similar adverse events including rigors and tremors

The following pre-specified symptoms, which were assessed on a daily basis during admission while admitted to the treatment unit, were reported in ≥40% of participants who received EBANGA: diarrhea, pyrexia, abdominal pain, and vomiting. Evaluation of these symptoms may have been confounded by the underlying Orthoebolavirus zairense infection.

Discontinuation and Infusion Rate Adjustments

Approximately 99% of participants who received EBANGA in the PALM trial were able to complete their dose within one hour. Two participants who received EBANGA (1%) did not receive their complete infusion. In eight participants (5%) the EBANGA infusion rate was decreased due to an AE [see Warnings and Precautions (5.1)].

Selected Laboratory Abnormalities in the PALM Trial

Table 3 presents selected laboratory abnormalities (worsening to Grade 3 or 4 compared to baseline) in the PALM trial.

Table 3 Selected Grade 3 and 4 Laboratory Abnormalitiesa, Worsened Grade from Baseline in the PALM Trial
Laboratory Testa | EBANGA N=173 % | Control N=168 %
Sodium, high ≥ 154 mmol/L | 5 | 4
Sodium, low < 125 mmol/L | 7 | 11
Potassium, high ≥ 6.5 mmol/L | 15 | 12
Potassium, low < 2.5 mmol/L | 6 | 8
Creatinine (mg/dL) > 1.8 × ULN or ≥ 1.5 × baseline b | 27 | 23
Alanine aminotransferase (U/L) ≥ 5 × ULNc | 12 | 14
Aspartate aminotransferase (U/L) ≥ 5 × ULNd | 13 | 18
ULN= upper limit of normal
a Graded per Division of AIDS (DAIDS) v2.1
b Based on a ULN of 1.2 mg/dL.
c Based on a ULN of 47 U/L.
d Based on a ULN of 38 U/L.

6.2 Immunogenicity

As with all therapeutic proteins, there is potential for immunogenicity from using ansuvimab-zykl. There are no data to assess the effects of potential immunogenicity on efficacy and safety in participants with Orthoebolavirus zairense infection.

7 DRUG INTERACTIONS

7.1 Vaccine Interactions

No vaccine-therapeutic interaction studies have been performed in human participants using EBANGA. However, because of the potential for EBANGA to inhibit replication of a live vaccine virus indicated for prevention of Orthoebolavirus zairense infection and possibly reduce the efficacy of the vaccine, avoid the concurrent administration of a live vaccine during treatment with EBANGA. The interval between administration of EBANGA therapy and live vaccination should be in accordance with current vaccination guidelines. The efficacy of EBANGA among participants who reported receipt of a recombinant live vaccine prior to their enrollment in the PALM trial was similar to participants who did not report receiving a vaccine prior to enrollment.

8 USE IN SPECIFIC POPULATIONS

8.1 Pregnancy

Risk Summary

Orthoebolavirus zairense infection is life-threatening for both the mother and fetus and treatment should not be withheld due to pregnancy (see Clinical Considerations). Available data from the PALM trial in which pregnant women with Orthoebolavirus zairense infection were treated with EBANGA demonstrate the high rate of maternal and fetal/neonatal morbidity consistent with published literature regarding the risk associated with underlying maternal Orthoebolavirus zairense infection. These data are insufficient to evaluate for a drug associated risk of major birth defects, miscarriage, or adverse maternal/fetal outcome.

Animal reproduction studies with ansuvimab-zykl have not been conducted. Monoclonal antibodies, such as EBANGA, are transported across the placenta; therefore, EBANGA has the potential to be transferred from the mother to the developing fetus.

Clinical Considerations

Disease-associated maternal and/or embryo/fetal risk

Maternal, fetal and neonatal outcomes are poor among pregnant women infected with Orthoebolavirus zairense. The majority of such pregnancies result in maternal death with miscarriage, stillbirth, or neonatal death. Treatment should not be withheld due to pregnancy.

8.2 Lactation

Risk Summary

The Centers for Disease Control and Prevention recommend that mothers with confirmed Orthoebolavirus zairense not breastfeed their infants to reduce the risk of postnatal transmission of Orthoebolavirus zairense infection.

There are no data on the presence of ansuvimab-zykl in human or animal milk, the effects on the breastfed infant, or the effects on milk production. Maternal IgG is known to be present in human milk. The effects of local gastrointestinal exposure and limited systemic exposure in the breastfed infant to ansuvimab-zykl are unknown.

8.4 Pediatric Use

The safety and effectiveness of EBANGA for the treatment of infection caused by Orthoebolavirus zairense have been established in pediatric patients from birth to less than 18 years of age. Use of EBANGA for this indication is supported by evidence from a multi-center, open label, randomized controlled trial of EBANGA in adults and pediatric participants that included 54 pediatric participants birth to less than 18 years of age, including neonates born to a mother who is RT-PCR positive for Orthoebolavirus zairense infection. Of the total number of participants administered EBANGA in the PALM trial, pediatric participants (1 day to 17 years) accounted for 31% (n=54) of the study population in the PALM trial. The 28-day mortality and safety in adult and pediatric participants treated with EBANGA were similar [see Adverse Reactions (6.1), and Clinical Studies (14)]. An additional 78 (31%) pediatric participants from birth to less than 18 years of age received EBANGA in an expanded access program.

8.5 Geriatric Use

Clinical trials of EBANGA did not include sufficient numbers of participants aged 65 and over to determine whether the safety profile of EBANGA is different in this population compared to younger participants. Of the total number of participants administered EBANGA in the PALM trial, 6 participants (3%) were 65 years or older. The limited clinical experience has not identified differences in responses between the elderly and younger participants.

11 DESCRIPTION

Ansuvimab-zykl is an Orthoebolavirus zairense (EBOV) glycoprotein 1 (GP1)-directed recombinant, human IgG1 monoclonal antibody. Ansuvimab-zykl is produced in Chinese Hamster Ovary (CHO) cells by recombinant DNA technology and has an approximate molecular weight of 147 kDa.

EBANGA (ansuvimab-zykl) for injection is a sterile, preservative-free, off-white to white lyophilized powder in a single-dose vial for IV use after reconstitution and dilution. Each single-dose vial delivers 400 mg of ansuvimab-zykl, and L-histidine (12.4 mg), L-histidine HCl (16.8 mg), polysorbate 80 (1.6 mg), and sucrose (657 mg). After reconstitution with 7.7 mL of Sterile Water for Injection, USP, each vial delivers 8 mL of a clear and colorless to slightly yellow solution containing 50 mg/mL of ansuvimab-zykl, with an approximate pH of 6.

12 CLINICAL PHARMACOLOGY

12.1 Mechanism of Action

Ansuvimab-zykl is a recombinant human monoclonal antibody with antiviral activity against Orthoebolavirus zairense [see Microbiology (12.4)].

12.2 Pharmacodynamics

Ansuvimab-zykl exposure-response relationship and the time course of pharmacodynamic response is unknown.

12.3 Pharmacokinetics

Limited data from 18 healthy participants 22 to 56 years of age suggests that the pharmacokinetic profile of ansuvimab-zykl is consistent with the profile of other IgG1 monoclonal antibodies.

Pharmacokinetic data are not available for Orthoebolavirus zairense infected patients.

Specific Populations

The effect of age, renal impairment or hepatic impairment on the pharmacokinetics of ansuvimab-zykl is unknown.

12.4 Microbiology

Mechanism of Action

EBANGA (ansuvimab-zykl) is a recombinant, human IgG1κ monoclonal antibody that binds to the glycan cap and inner chalice of the EBOV GP1 subunit. The epitope to which it binds is located within the receptor binding domain of EBOV consisting of amino acids LEIKKPDGS (GP residues 111–119).

Ansuvimab-zykl binds EBOV GP without the mucin-like domain with a KD of 0.2 nM at pH 7.4 and 0.6 nM at pH 5.3 as measured by biolayer interferometry. Ansuvimab-zykl blocks binding of EBOV GP1 to the Neiman Pick cell receptor 1 in host cells (half-maximal effective concentration (EC50) value of 0.09 μg/mL), inhibiting virus entry into the host cell. Ansuvimab-zykl exhibited Fc-mediated Antibody Dependent Cellular Cytotoxicity (ADCC) activity against cells expressing EBOV GP when effector cells were added.

Antiviral Activity

In a live virus plaque-reduction neutralization assay performed in Vero E6 cells, ansuvimab-zykl neutralized Orthoebolavirus zairense Mayinga with an EC50 value of 0.06 µg/mL. In a pseudotyped EBOV GP lentivirus infectivity assay using HEK293 cells, ansuvimab-zykl inhibited Orthoebolavirus zairense Mayinga with an EC50 value of 0.09 μg/mL and Orthoebolavirus zairense Makona with an EC50 value of 0.15 μg/mL. The ADCC activity of ansuvimab-zykl was assessed in EBOV GP-transduced and non-transduced HEK293T target cells in the presence of antibody with effector cells added at an effector-to-target cell ratio 1:50 and analyzed via flow cytometry. Ansuvimab-zykl mediated ADCC, with maximal activity observed at mAb concentration of 0.03 μg/mL. Treatment of Orthoebolavirus zairense infected rhesus macaques with a single IV dose of ansuvimab-zykl (50 mg per kg) generally protected infected animals from Orthoebolavirus zairense mediated death when drug was administered 5 days post-infection.

Antiviral Resistance

No in-vivo nonclinical or clinical studies specifically evaluating resistance to ansuvimab-zykl have been conducted. The possibility of resistance to ansuvimab-zykl should be considered in patients who either fail to respond to therapy or who develop relapse of disease after an initial period of responsiveness.

Cell Culture Resistance

Ansuvimab-zykl cell culture resistance studies have been performed using replication competent recombinant vesicular stomatitis virus expressing the EBOV surface glycoprotein (rVSV-EBOV GP). The rVSV-EBOV GP virus was sequentially sub-cultured in six experiments for up to 5 passages in the presence of a concentration range of ansuvimab-zykl (0.08 to 50 µg/mL) to determine if escape mutants developed via selective pressure. A total of seven different amino acid substitutions in the EBOV GP were found (Table 4). Three of the seven were detected at less than 1% sequence frequency and were not within the ansuvimab-zykl GP epitope or within 5Å of the epitope, and therefore were excluded from further analysis.

Table 4 Identification of Ebola GP Substitutions in Cell Culture Studies
GP Substitutions | % Frequency of Sequences with the Substitutiona | Ansuvimab-zykl Amino Acid Substitutions Selected at 50 µg/mL
R29S | <1 | Excluded
P116H | 71–94 | Resistant
T144M | 71–100 | Resistant
N228H | <1 | Excluded
R299K | 71 | No Resistance - Equivalent ansuvimab-zykl neutralization to Kikwit reference GP sequence
N434K | 73 | No Resistance - Equivalent ansuvimab-zykl neutralization to Kikwit reference GP sequence
T634A | <1 | Excluded
a Frequency range of the sequences in 6 replicate experiments identified at the highest ansuvimab-zykl concentration of 50 µg/mL

The four remaining GP amino acid substitutions (P116H, T144M, R299K and N434K) were further evaluated in a single-cycle neutralization assay using a replication-defective lentiviral vector not expressing envelope pseudotyped with EBOV GP containing each of the substitutions. The P116H and T144M substitutions exhibited resistance to ansuvimab-zykl based on no neutralization detected at the highest concentrations assessed (10 µg/mL) resulting in a >56-fold reduction in susceptibility for each substitution compared to the wild type EBOV GP.

Two additional substitutions within the EBOV GP conserved region (G118E and G118R), which were not found in the studies described above, have been reported in the literature from similar cell culture resistance studies and these substitutions were able to confer >29- and >34-fold reductions in susceptibility to ansuvimab-zykl, respectively.^1

Of the four resistant substitutions identified under selective pressure in cell culture (P116H, G118E, G118R, and T144M), only G118R has been identified in naturally infected Ebola virus disease patients in low frequency through NGS sequencing.

In Clinical Studies

A post-hoc detailed analysis of currently available EBOV GP sequences in the public database (as of November 2022) was performed to identify all amino acid polymorphisms in the ansuvimab-zykl epitope (GP positions 111-119) and amino acids within 5Å of the epitope. A total of nine sequences out of 3324 available EBOV genomes had amino acid changes, of which two were within the ansuvimab-zykl linear epitope (L111I and L111F) and two within 5Å of the epitope compared to the Kikwit variant (I170L and I170F). Of the nine EBOV GP sequences, six were at the same amino acid location with the same amino acid substitution (I170L), one was at the same location as the previous six, but with a different amino acid substitution (I170F). The remaining two were at the same location but with different amino acid substitutions (L111I and L111F). Overall, four of the nine EBOV GP sequences expressed distinct amino acid substitutions at only two different positions. Phenotypic assessments of these amino acid changes inside of, or within 5Å of the ansuvimab-zykl linear epitope (111-119) were performed with a single-cycle neutralization assay using a replication-defective lentiviral vector not expressing envelope pseudotyped with EBOV GP containing each of the substitutions. The EBOV-GP pseudotyped lentiviral vectors with the I170F and I170L substitutions were found to be inactive and unable to infect target cells. EBOV-GP pseudotyped lentiviral vectors with the L111I and L111F were fully neutralized by ansuvimab-zykl with a potency similar to the Ituri wild type variant and historic Mayinga variant EC50 values and therefore none of the four identified amino acid substitutions are expected to be resistant to ansuvimab-zykl.

PALM Clinical study and MEURI EAP

Samples from a total of 95 participants (79 participants enrolled in the PALM randomized controlled clinical study and 16 participants from the MEURI EAP) including samples from 40 deceased participants and from 36 surviving participants with paired samples taken at baseline (pre-treatment) and after treatment with ansuvimab-zykl where available for EBOV glycoprotein (GP) sequencing. A total of 147 EBOV (GP) genome sequences were produced. When compared to the Kikwit and the Ituri variants, 26 and 14 amino acid substitutions, respectively, were found outside of the region of the ansuvimab-zykl epitope in EBOV GP from PALM trial participants. These amino acid changes were located predominantly in the less conserved mucin-like domain of the EBOV GP. None of these amino acid changes were associated with mortality nor appeared to be driven by ansuvimab-zykl treatment.

The amino acid substitution G118R, which was identified in cell culture selection experiments and had a >34-fold reduction in susceptibility to ansuvimab-zykl, was detected at 9% to 13% frequency by Next Generation Sequencing (NGS) in 10 participant samples (9 of which were survivors) collected prior to treatment with ansuvimab-zykl in the PALM and MEURI EAP^1; the clinical significance of this substitution is unknown.

Additional post-hoc analysis of NGS data from the viral sequences detected several amino acid substitutions located in the ansuvimab-zykl epitope (K115, P116L, D117G) and within 5Å of the ansuvimab-zykl epitope (Y109C/H, L122P/S, V141A, P146L, C147K, Y171C, F176L). These substitutions, along with two controls that have known resistance (L111F, P116H), were evaluated for reductions in susceptibility to ansuvimab-zykl in comparison to the wild-type EBOV (Mayinga strain) using EBOV GP pseudotyped virus-like particle (PsVLP) infection of HEK293T cells. Out of the 18 PsVLPs produced (including the two controls), P116L showed significant reductions in susceptibility to ansuvimab-zykl, resulting in a mean 29.2-fold change compared to the wild-type EBOV GP. Three substitutions (K115N, D117G, and P146L) exhibited a range of 3.2- to 4.3-fold reduction in susceptibility based on mean reductions relative to wild-type control. Infectivity of the variants in this analysis ranged from 0.21 to 0.86 (where wild-type EBOV infectivity = 1). Table 5 provides an overview of the infectivity and fold change of the four variants and two controls from this analysis. The clinical significance of these substitutions is unknown.

Table 5 Infectivity and Mean Reductions in Susceptibility in Cell Culture of Select Ebolavirus Glycoprotein (EBOV GP) Variants (Pseudotyped Virus-Like Particles) compared to Wild-Type EBOV
EBOV GP Varianta | Infectivityb | Mean Fold Changeb
L111F (control) | 0.90 | 2.6
K115N | 0.31 | 4.3
P116H (control) | 0.80 | N/Ac
P116L | 0.75 | 29.2
D117G | 0.86 | 3.2
P146L | 0.21 | 3.2
N/A = Not applicable.
a The pseudotyped virus-like particle variants K115N, P116L and D117G contain amino acid substitutions at the Ebanga EBOV GP target epitope; while variant P146L is within 5 Å of the Ebanga EBOV GP target epitope.
b Infectivity and reductions in susceptibility values are relative to wild-type (WT) EBOV (Mayinga strain). Relative Infectivity values of <1 indicates the variant exhibits lower infectivity compared to the WT (WT Infectivity =1).
c There was no neutralization detected at the highest concentration evaluated (18 µg/mL) for control variant P116H.

Immune Response

Interaction studies with recombinant live EBOV vaccines and EBANGA have not been conducted [see Drug Interactions (7.1)].

13 NONCLINICAL TOXICOLOGY

13.1 Carcinogenesis, Mutagenesis, Impairment of Fertility

Carcinogenicity, genotoxicity and fertility studies have not been conducted with ansuvimab-zykl.

14 CLINICAL STUDIES

The efficacy of EBANGA has been evaluated in 174 participants with confirmed Orthoebolavirus zairense infection in the PALM trial, a multi-center, open-label, randomized, controlled trial (NCT03719586). The trial was conducted in the North Kivu and Ituri provinces in the Democratic Republic of Congo, where an outbreak began in August 2018, and enrolled 681 participants of all ages, including pregnant women, with documented Orthoebolavirus zairense infection and symptoms of any duration who were receiving oSOC. Eligible participants had a positive reverse transcriptase-polymerase chain reaction (RT-PCR) for the nucleoprotein (NP) gene of Orthoebolavirus zairense and had not received other investigational treatments (with the exception of experimental vaccines) within the previous 30 days. Neonates ≤7 days of age were eligible if the mother had documented infection. Neonates born to a mother who had cleared Orthoebolavirus zairense following a course of her assigned investigational medication were also eligible to be enrolled at investigator discretion regarding the likelihood that the neonate was infected. Participants were randomized to receive EBANGA 50 mg/kg IV as a single infusion, an investigational control 50 mg/kg IV every third day, for a total of 3 doses, or other investigational drugs. Randomization was stratified by reverse transcription-PCR cycle threshold calculated using NP targets (CtNP ≤22.0 vs ˃22.0; corresponding to high and low viral load, respectively) and Ebola Treatment Unit (ETU) site. All participants received oSOC consisting, at a minimum, of IV fluids, daily clinical laboratory testing, correction of hypoglycemia and electrolyte imbalances, and broad-spectrum antibiotics and antimalarials, as indicated.

The primary efficacy endpoint was 28-day mortality. The primary analysis population includes all participants who were randomized and concurrently eligible to receive either EBANGA or the investigational control during the same time period of the trial.

The demographics and baseline characteristics are provided in Table 6 below.

Table 6 Demographics and Baseline Characteristics in PALM Trial
Parameter | EBANGA N=174 N (%) | Control N=168 N (%)
Mean age (years) | 27.3 | 29.9
Age <1 month, n (%) | 4 (2) | 2 (1)
Age 1 month to <1 year, n (%) | 7 (4) | 5 (3)
Age 1 year to <6 years, n (%) | 15 (9) | 12 (7)
Age 6 years to <12 years, n (%) | 13 (7) | 5 (3)
Age 12 years to <18 years, n (%) | 15 (9) | 9 (5)
Age 18 years to <50 years, n (%) | 93 (53) | 114 (68)
Age 50 years to <65 years, n (%) | 21 (12) | 18 (11)
Age ≥65 years, n (%) | 6 (3) | 3 (2)
Female, n (%) | 98 (56) | 87 (52)
Positive result on pregnancy testa, n (%) | 5/98 (5) | 4/87 (5)
RT-PCR CtNP cycle threshold ≤22, n (%) | 73 (42) | 70 (42)
Median RT-PCR CtNP (IQR) | 23.3 (19.7, 28.5) | 23.1 (19.0, 26.5)
Median creatinine (IQR) | 0.9 (0.6, 2.4) | 1.2 (0.8, 4.3)
Median AST (IQR) | 234 (66, 978) | 351 (112, 1404)
Median ALT (IQR) | 168 (44, 551) | 236 (48, 631)
Median days from onset of symptoms to randomization (IQR) | 5 (3, 7) | 5 (3, 7)
Reported Vaccination with rVSV-ZEBOV vaccine, n (%) | 36 (21) | 41 (24)
<10 days before ETU admission, n (%) | 22/36 (61) | 21/41 (51)
≥10 days before ETU admission, n (%) | 12/36 (33) | 18/41 (44)
Timing unknown, n (%) | 2/36 (6) | 2/41 (5)
a Pregnancy positive test was calculated based on participants who were pregnant. Denominator for percentages is the number of females in the treatment group.
CtNP = cycle threshold calculated using NP targets; IQR=interquartile range; AST=Aspartate aminotransferase; ALT=Alanine aminotransferase; ETU=Ebola treatment unit.

The PALM trial was stopped early on the basis of a pre-specified interim analysis showing a statistically significant reduction in mortality for EBANGA compared to control assessed at Day 28.

Mortality efficacy results are shown in Table 7 and Figure 1.

Table 7 Mortality Rates in PALM Trial
Efficacy Endpoints | EBANGAa N=174 | Controla N=168
Overall
28-day mortality, n (%) | 61 (35%) | 83 (49%)
Mortality rate difference relative to control (95% CI)b | -14.3 (-24.7, -3.7)
p-Valuec | 0.008
Baseline Viral Load
High viral load (CtNP ≤ 22)d
28-day mortality, n (%) | 51/73 (70%) | 60/70 (86%)
Mortality rate difference relative to control (95% CI)b | -15.9 (-31.6, 0.9)
Low viral load (CtNP > 22)d
28-day mortality, n (%) | 10/101 (10%) | 23/97 (24%)
Mortality rate difference relative to control (95% CI)b | -13.8 (-27.3, 0.3)
Age group, 28-day mortality, n/N (%)
Adults (age ≥18 years) | 41/120 (34%) | 68/135 (50%)
12 to < 18 years of age | 5/15 (33%) | 5/9 (56%)
6 to < 12 years of age | 4/13 (31%) | 2/5 (40%)
< 6 years of age | 11/26 (42%) | 8/19 (42%)
Sex, 28-day mortality, n/N (%)
Male | 30/76 (39%) | 32/81 (40%)
Female | 31/98 (32%) | 51/87 (59%)
N=Number of participants in the Concurrent Intention-to-Treat population and treatment group; n=Number of participants with the 28-day outcome. Denominator for percentages is the total number of participants in the specific group.
a Both EBANGA and Control were administered with optimized standard of care
b 95% CI for Difference = 95% confidence intervals were computed by inverting two one-sided exact tests.
c The result is significant according to the interim stopping boundary, p<0.028.
d Cepheid GeneXpert Ebola® Assay used for detection of Orthoebolavirus zairense RNA

Figure 1: Kaplan-Meier Curve for Overall Mortality in PALM Trial

15 REFERENCES

1. Rayaprolu V, Fulton BO, Rafique A, Arturo E, Williams D, Hariharan C, Callaway H, Parvate A, Schendel SL, Parekh D, Hui S, Shaffer K, Pascal KE, Wloga E, Giordano S, Negron N, Ni M, Copin R, Atwal GS, Franklin M, Boytz RM, Donahue C, Davey R, Baum A, Kyratsous CA, Saphire EO. Structure of the Inmazeb Cocktail and Resistance to Ebola Virus Escape. Cell Host Microbe. 2023 Feb 8;31(2):260-272.e7. doi: 10.1016/j.chom.2023.01.002.

16 HOW SUPPLIED / STORAGE AND HANDLING

How Supplied

EBANGA (ansuvimab-zykl) for injection is supplied as a sterile, preservative-free, off-white to white lyophilized powder in a single-dose vial (NDC 71655-578-01) for reconstitution and further dilution.

One primary carton (NDC 71655-578-02) contains thirty-six 400 mg vials packaged in a box containing either one primary carton (NDC 71655-578-03), four primary cartons (NDC 71655-578-04), or eight primary cartons (NDC 71655-578-08).

Storage and Handling

Store refrigerated at 2ºC to 8ºC (36ºF to 46ºF) in the original carton to protect from light. Do not freeze. Do not shake.

Prior to reconstitution, allow EBANGA vial(s) to reach ambient temperature (15°C to 27°C [59°F to 81°F]) for approximately 20 minutes. If for any reason reconstitution cannot proceed immediately upon reaching ambient temperature, vials that have NOT been reconstituted may be kept at ambient temperature, protected from light, for no more than 24 hours.

After reconstitution, if storage is needed, the entire storage time for the reconstituted solution in the vial and the diluted solution in the IV bag should be protected from light and limited to 4 hours refrigerated at 2°C to 8°C (36°F to 46°F) [see Dosage and Administration (2.2)].

17 PATIENT COUNSELING INFORMATION

Hypersensitivity Reactions Including Infusion-Associated Events

Inform patients that hypersensitivity reactions including infusion-associated events have been reported during and post-infusion with EBANGA and to immediately report if they experience any symptoms of systemic hypersensitivity reactions [see Warnings and Precautions (5.1)].

Lactation

Instruct patients with Orthoebolavirus zairense not to breastfeed because of the risk of passing Orthoebolavirus zairense to the baby [see Use in Specific Populations (8.2)].

Manufactured by:

Emergent Manufacturing Operations Baltimore LLC
5901 East Lombard St.
Baltimore, MD 21224
U.S. Lic. No. 2083

EBANGA™ is a trademark of Ridgeback Biotherapeutics, LP
EBANGA™ is protected by one or more claims of U.S. Patent 10, 160, 795
© 2025 Emergent Manufacturing Operations Baltimore LLC. All rights reserved.

PRINCIPAL DISPLAY PANEL – 400 mg vial label

NDC 71655-578-01

ebanga TM
(ansuvimab-zykl)

for Injection

400 mg per vial

For Intravenous Use. Reconstitute and dilute prior to administration.

Rx Only

Recommended Dosage: See prescribing information.

Single-Dose Vial. Discard Unused Portion.

Store at 2°C to 8°C (36°F to 46°F). Protect from light. Do not freeze. Do not shake.

Mfg by: Emergent Manufacturing operations Baltimore LLC, Baltimore, MD 21224

U.S. Lic. No. 2083

PRINCIPAL DISPLAY PANEL – Carton containing 36x400 mg vials

NDC 71655-578-02 Rx only

ebangaTM
(ansuvimab-zykl)
For Injection

400 mg per vial

For intravenous use

Contents: 36 x 400 mg vials

PRINCIPAL DISPLAY PANEL – Box containing single carton

NDC 71655-578-03 Rx only

ebangaTM
(ansuvimab-zykl)
For injection

400 mg per vial

For Intravenous use

Contents: 1 x 36 x 400 mg vials

PRINCIPAL DISPLAY PANEL – Box containing 4 cartons

NDC 71655-578-04 Rx only

ebangaTM
(ansuvimab-zykl)
For injection

400 mg per vial

For Intravenous use

Contents: 4 x 36 x 400 mg vials

PRINCIPAL DISPLAY PANEL – Box containing 8 cartons

NDC 71655-578-08 Rx only

ebangaTM
(ansuvimab-zykl)
For injection

400 mg per vial

For Intravenous use

Contents: 8 x 36 x 400 mg vials